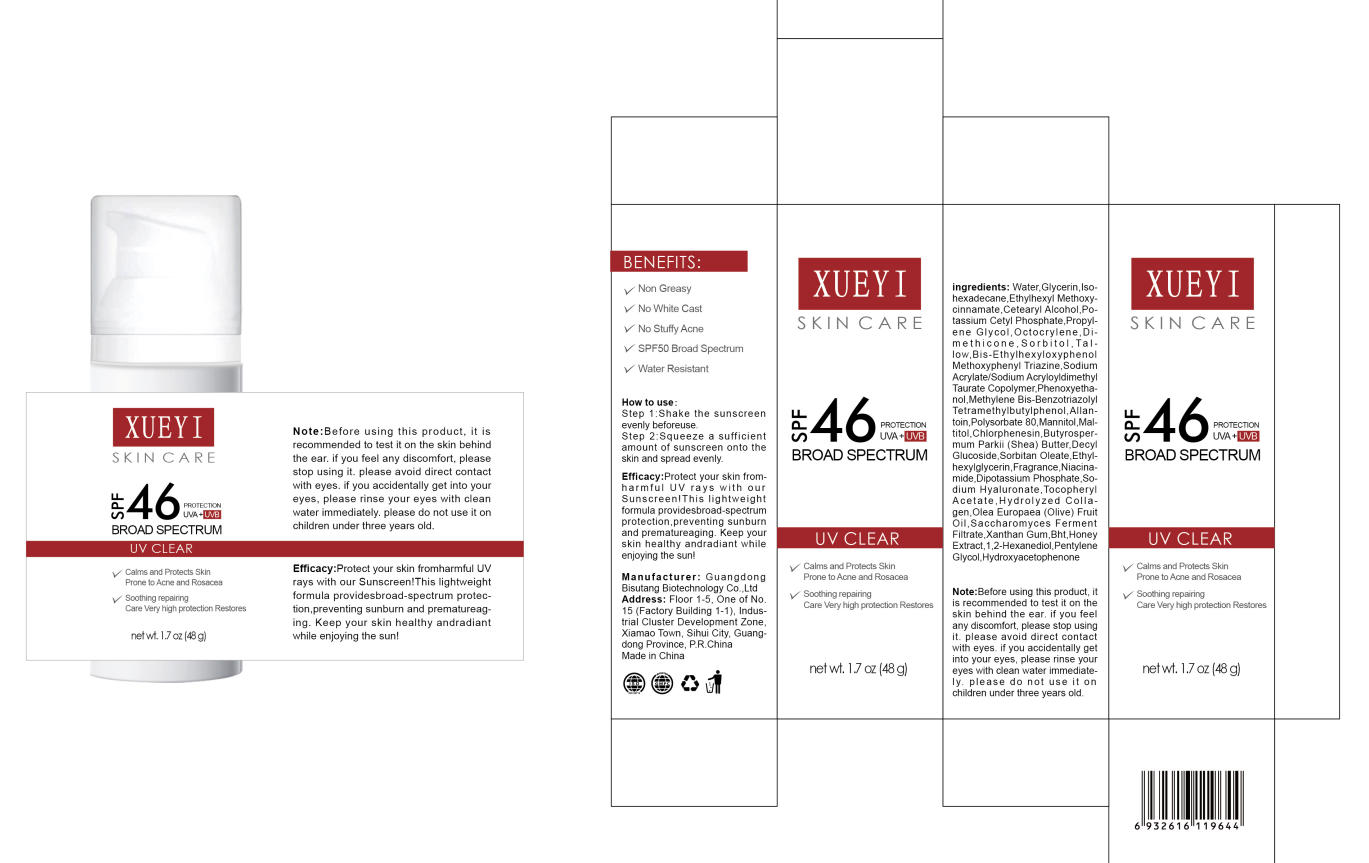 DRUG LABEL: XUEYI SKIN CARE SUNSCREEN
NDC: 84753-037 | Form: CREAM
Manufacturer: Guangdong Bisutang Biotechnology Co., LTD
Category: otc | Type: HUMAN OTC DRUG LABEL
Date: 20250922

ACTIVE INGREDIENTS: OCTOCRYLENE 3 mg/100 g; METHYLENE BIS-BENZOTRIAZOLYL TETRAMETHYLBUTYLPHENOL 0.75 mg/100 g; ETHYLHEXYL METHOXYCINNAMATE 5.9958 mg/100 g; 4-METHYLBENZYLIDENE CAMPHOR 2 mg/100 g; PHENYLBENZIMIDAZOLE SULFONIC ACID 1 mg/100 g; HONEY 0.001 mg/100 g; SACCHAROMYCES LYSATE 0.00885 mg/100 g; HYDROLYSED MARINE COLLAGEN (ENZYMATIC; 2000 MW) 0.01 mg/100 g
INACTIVE INGREDIENTS: SORBITAN OLEATE; BUTYROSPERMUM PARKII (SHEA) BUTTER; WATER; CETEARYL ALCOHOL; SODIUM ACRYLATE; MALTITOL; DMDM HYDANTOIN; METHYLPARABEN; ALPHA-TOCOPHEROL ACETATE; FRAGRANCE MINT ORC2000774; GLYCERIN; PENTYLENE GLYCOL; TALLOW; ETHYLHEXYL PALMITATE; MANNITOL; 1,2-HEXANEDIOL; ALLANTOIN; ZINC OXIDE; CI 11680; CAPRYLYL GLYCOL; SORBITOL; BHT; DECYL GLUCOSIDE; SODIUM LAURETH SULFATE; XANTHAN GUM; POTASSIUM CETYL PHOSPHATE; OLEA EUROPAEA (OLIVE) FRUIT OIL; POLYSORBATE 80; PROPYLENE GLYCOL 1,2-DISTEARATE; HYDROXYACETOPHENONE; DIMETHICONE; PHENOXYETHANOL; ISOHEXADECANE

DIRECTIONS:

- Apply liberally 15 minutes before sun exposure

- Reapply at least every 2 hours

- Use a water resistant sunscreen if swimming or sweating

- Children under 6 months of age: ask a doctor

INACTIVE INGREDIENT

WATER
BHT
GLYCERIN
ETHYLHEXYL PALMITATE
CETEARYL ALCOHOL
SODIUM ACRYLATE/SODIUM ACRYLOYLDIMETHYL TAURATE COPOLYMER
ISOHEXADECANE
POLYSORBATE 80
SORBITAN OLEATE
DECYL GLUCOSIDE
PROPYLENE GLYCOL
XANTHAN GUM
POTASSIUM CETYL PHOSPHATE
DIPOTASSIUM PHOSPHATE
SORBITOL
MANNITOL
MALTITOL
DIMETHICONE
DMDM HYDANTOIN
ALLANTOIN
METHYLPARABEN
BUTYROSPERMUM PARKII (SHEA) BUTTER
FRAGRANCE
HYDROXYACETOPHENONE
PENTYLENE GLYCOL
1,2-HEXANEDIOL
TOCOPHERYL ACETATE
OLEA EUROPAEA (OLIVE) FRUIT OIL
TALLOW
ZINC OXIDE
CI 11680
SODIUM LAURETH SULFATE
PHENOXYETHANOL
CAPRYLYL GLYCOL

USES:

- Helps prevent sunburn.
- If used as directed with other sun protection measures (see Directions), decreases the risk of skin cancer and early skin aging caused by the sun.

ACTIVE INGREDIENT

ETHYLHEXYL METHOXYCINNAMATE
OCTOCRYLENE
4-METHYLBENZYLIDENE CAMPHOR
METHYLENE BIS-BENZOTRIAZOLYL TETRAMETHYLBUTYLPHENOL
PHENYLBENZIMIDAZOLE SULFONIC ACID
SACCHAROMYCES FERMENT FILTRATE
HONEY EXTRACT
HYDROLYZED COLLAGEN

Keep out of reach of children. If swallowed, get medical help or contact a Poison Control Center right away.

PURPOSE

Sunscreen

WARNINGS:

- For external use only.